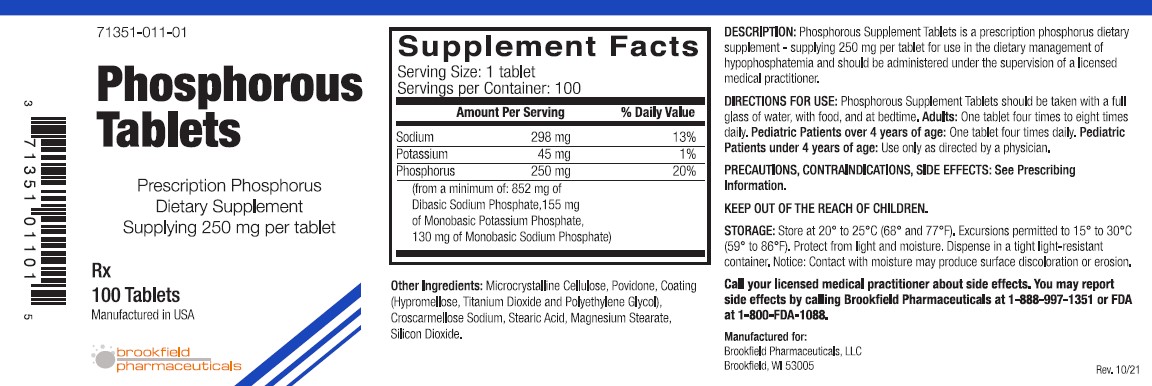 DRUG LABEL: Phosphorous Dietary Supplement
NDC: 71351-011 | Form: TABLET
Manufacturer: BROOKFIELD PHARMACEUTICALS, LLC
Category: other | Type: Dietary Supplement
Date: 20231012

ACTIVE INGREDIENTS: SODIUM PHOSPHATE, DIBASIC, UNSPECIFIED FORM 852 mg/1 1; MONOBASIC POTASSIUM PHOSPHATE 155 mg/1 1; SODIUM PHOSPHATE, MONOBASIC, UNSPECIFIED FORM 130 mg/1 1
INACTIVE INGREDIENTS: CELLULOSE, MICROCRYSTALLINE; POVIDONE; HYPROMELLOSE, UNSPECIFIED; TITANIUM DIOXIDE; POLYETHYLENE GLYCOL, UNSPECIFIED; CROSCARMELLOSE SODIUM; STEARIC ACID; MAGNESIUM STEARATE; SILICON DIOXIDE

Phosphorous Tablets

STATEMENT OF IDENTITY

Phosphorus Dietary Supplement -supplying 250 mg per tablet
71351-011-01

DESCRIPTION
Phosphorous Tablets is a prescription phosphorus dietary supplement - supplying 250 mg phosphorus per tablet for use in the dietary management of hypophosphatemia and should be administered under the supervision of a licensed medical practitioner.

Supplement Facts
Serving Size: 1 tablet
Servings per Container: 100
 | Amount per Serving | %Daily Value
Sodium | 298 mg | 13%
Potassium | 45 mg | 1%
Phosphorus | 250 mg | 20%
(from a minimum of: 852 mg of Dibasic Sodium Phosphate, 155 mg of Monobasic Potassium Phosphate, 130 mg of Monobasic Sodium Phosphate)

Other Ingredients
Microcrystalline Cellulose, Povidone, Coating (Hypromellose, Titanium Dioxide and Polyethylene Glycol), Croscarmellose Sodium, Stearic Acid, Magnesium Stearate, Silicon Dioxide.

INDICATIONS AND USAGE

As a phosphorus supplement, each tablet supplies 20% of the U.S. Recommended Daily Allowance (U.S. RDA) of phosphorus for adults and
children over 4 years of age. Phosphorous Tablets increases urinary phosphate and pyrophosphate.

Contraindications
This product is contradicted in patients with infected phosphate stones in the urinary tract, in patients with severely impaired renal function (less than 30% of normal) and in the presence of hyperphosphatemia.

PRECAUTIONS

General
This product contains potassium and sodium and should be used with caution if clinical management of these elements is desired. Some individuals may experience a mild laxative effect during the first few days of phosphate supplementation; lower the daily dose until this effect subsides or, if necessary, discontinue the use of the product. Caution should be exercised when prescribing this product in the following conditions: Cardiac disease (particularly in patients receiving digitalis); severe adrenal insufficiency (Addison's disease); acute dehydration; severe renal insufficiency; renal function impairment or chronic renal disease; extensive tissue breakdown (such as with severe burns); myotonia congenita; cardiac failure; cirrhosis of the liver or severe hepatic disease; peripheral or pulmonary edema; hypernatremia; hypertension; toxemia of pregnancy, hypoparathyroidism; and acute pancreatitis. High serum phosphate levels may increase the incidence of extraskeletal calcification.

Information for Patients
Patients with kidney stones may pass old stones when phosphate supplementation is started and should be warned of this possibility. Patients should be advised to avoid the use of antacids containing aluminum, magnesium, or calcium because they may prevent the absorption of phosphate.

Laboratory Tests
Careful monitoring of renal function and serum calcium, phosphorus, potassium, and sodium may be required at periodic intervals during phosphate supplementation. Other tests may be warranted in some patients, depending on conditions.

Drug Interactions The use of antacids containing magnesium, aluminum, or calcium in conjunction with phosphate preparations may bind the phosphate and prevent its absorption. Concurrent use of antihypertensive drugs or corticosteroids with sodium phosphate may result in hypernatremia. Calcium-containing preparations and/or Vitamin D may antagonize the effects of phosphates in the treatment of hypercalcemia. Potassium-containing medication or potassium-sparing diuretics may cause hyperkalemia. Patients should have serum potassium level determinations at periodic intervals.

Carcinogenesis, Mutagenesis, Impairment of Fertility
No long term or reproduction studies in animals or humans have been performed with Phosphorous Tablets to evaluate its carcinogenic, mutagenic, or impairment of fertility potential.

Pregnancy and Lactation
Animal reproduction studies have not been conducted with Phosphorous Tablets. It is also not known whether this product can cause fetal harm when administered to a pregnant woman or can affect reproductive capacity. This product should be given to a pregnant woman only if clearly needed.
It is not known whether this product is excreted in human milk. Because many substances are excreted in human milk, caution should be exercised when this product is administered to a nursing woman.

Pediatric Use: See DIRECTIONS FOR USE.

SIDE EFFECTS

Gastrointestinal upset (diarrhea, nausea, stomach pain, or vomiting) may occur with phosphate supplementation. Bone and joint pain and possibly osteomalacia could occur.

Adverse effects due to sodium or potassium may be observed: headache; dizziness; mental confusion; seizures; weakness or heaviness of legs; unusual tiredness or weakness; numbness, tingling, pain or weakness of hands or feet; numbness or tingling around lips; fast or irregular heartbeat; shortness of breath or troubled breathing; swelling of feet or lower legs; unusual weight gain; low urine output; unusual thirst.

DIRECTIONS FOR USE

Phosphorous Supplement Tablets should be taken with a full glass of water, with food, and at bedtime.

Adults: One tablet four times to eight times daily.
Pediatric patients over 4 years of age: One tablet four times daily.
Pediatric Patients under 4 years of age: Use only as directed by a licensed physician.

STORAGE

Store at 20° to 25°C (68° to 77°F). Excursions permitted to 15° to 30°C (59° to 86°F). Protect from light and moisture. Dispense in a tight, light-resistant container.

HOW SUPPLIED
Phosphorous Tablets is supplied as white tablet dispensed in bottles of 100 tablets.
71351-011-01

WARNINGS

KEEP THIS OUT OF REACH OF CHILDREN
Call your licensed medical practitioner about side effects. You may report side effects by calling Brookfield Pharmaceuticals at
1-888-997-1351 or FDA at 1-800-FDA-1088.

Manufactured for:
Brookfield Pharmaceuticals, LLC
Brookfield, Wl 53005

MADE IN USA

Rev. 10/21